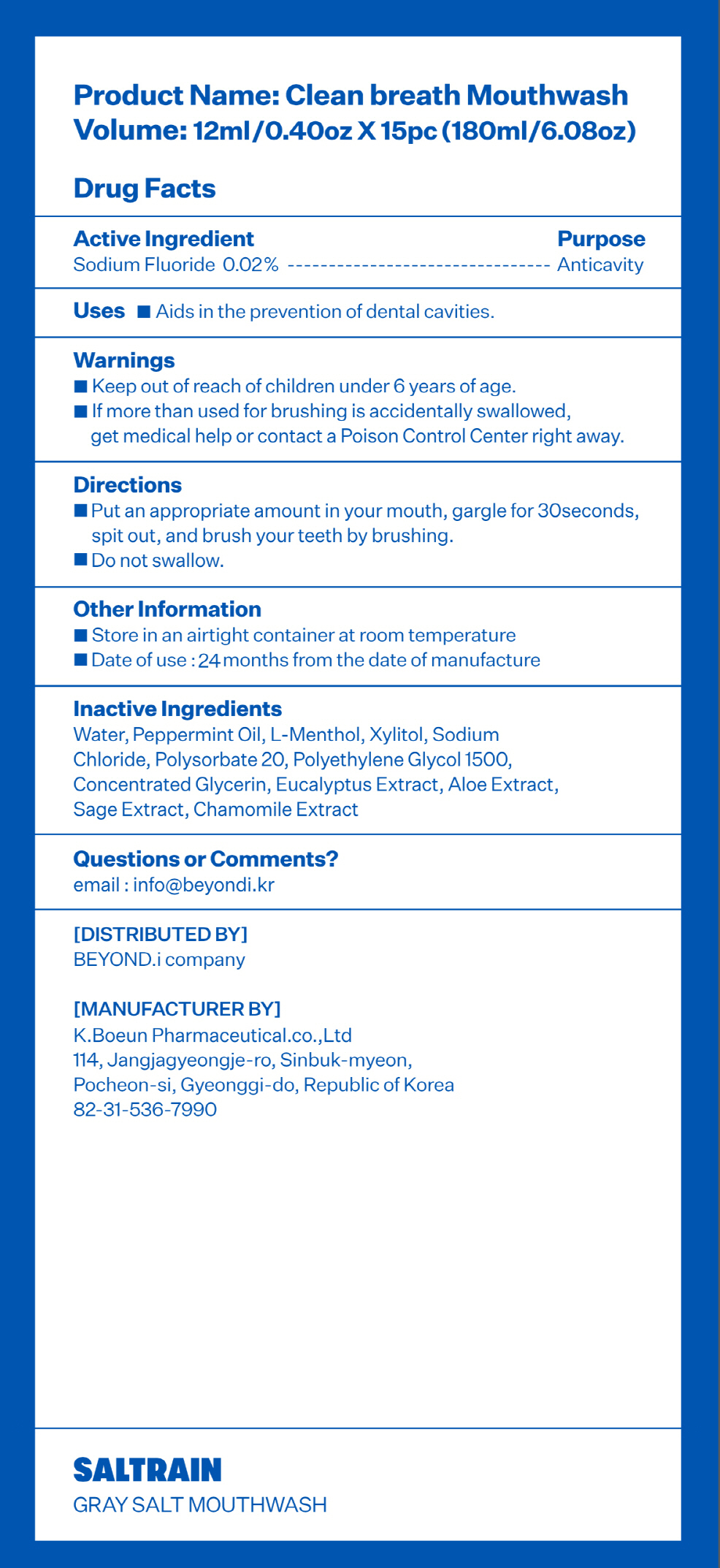 DRUG LABEL: SALTRAIN CLEAN BREATH
NDC: 74724-0020 | Form: MOUTHWASH
Manufacturer: K.Boeun Pharmaceutical Co.,Ltd.
Category: otc | Type: HUMAN OTC DRUG LABEL
Date: 20201110

ACTIVE INGREDIENTS: SODIUM FLUORIDE 0.02 g/100 mL
INACTIVE INGREDIENTS: SODIUM CHLORIDE; XYLITOL; WATER

ACTIVE INGREDIENT

Sodium Flouride

PURPOSE

For dental care

Keep out of reach of children

INDICATIONS AND USAGE

Put an appropriate amount in your mouth, gargle for 30 seconds, spit out, and brush your teeth by brushing

Do not swallow

Keep out of reach of children under 6 years old.

If more than used for brushing is accidentally swallowed, get medical help or contact a Poison Control Center right away.

INACTIVE INGREDIENT

Concentrated Glycerin, Polyethylene Glycol 1500, Polysorbate 20, Xylitol, Sodium Chloride, I-Menthol, Mentha Oil, Sage Extract, Aloe Extract, Eucalyptus Extract, Water

DOSAGE AND ADMINISTRATION

For dental use only